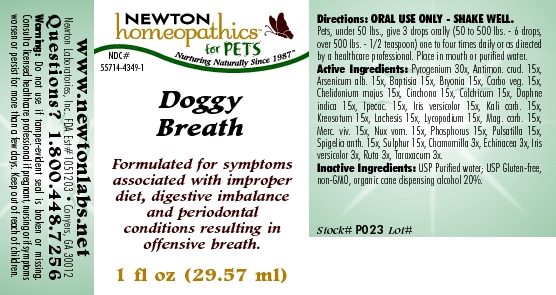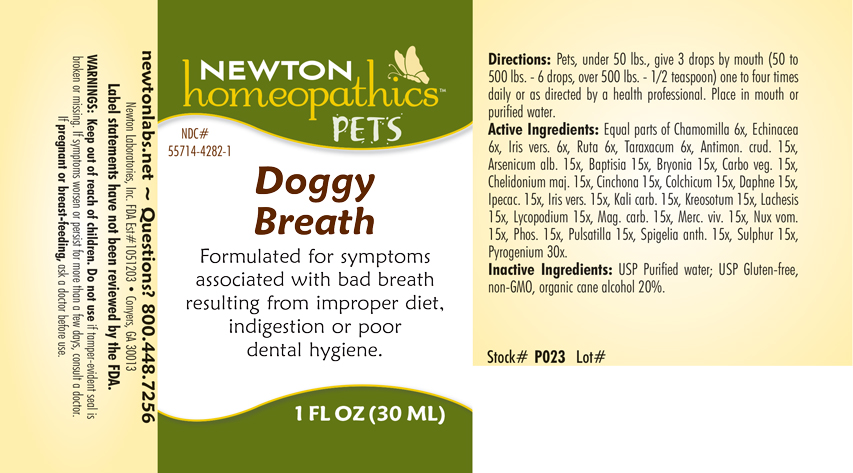 DRUG LABEL: Doggy Breath
NDC: 55714-4349 | Form: LIQUID
Manufacturer: Newton Laboratories, Inc.
Category: homeopathic | Type: OTC ANIMAL DRUG LABEL
Date: 20190114

ACTIVE INGREDIENTS: Rancid Beef 30 [hp_X]/1 mL; Antimony Trisulfide 15 [hp_X]/1 mL; Arsenic Trioxide 15 [hp_X]/1 mL; Baptisia Tinctoria 15 [hp_X]/1 mL; Bryonia Alba Root 15 [hp_X]/1 mL; Activated Charcoal 15 [hp_X]/1 mL; Chelidonium Majus 15 [hp_X]/1 mL; Cinchona Officinalis Bark 15 [hp_X]/1 mL; Colchicum Autumnale Bulb 15 [hp_X]/1 mL; Daphne Odora Bark 15 [hp_X]/1 mL; Ipecac 15 [hp_X]/1 mL; Iris Versicolor Root 15 [hp_X]/1 mL; Potassium Carbonate 15 [hp_X]/1 mL; Wood Creosote 15 [hp_X]/1 mL; Lachesis Muta Venom 15 [hp_X]/1 mL; Lycopodium Clavatum Spore 15 [hp_X]/1 mL; Magnesium Carbonate 15 [hp_X]/1 mL; Mercury 15 [hp_X]/1 mL; Strychnos Nux-vomica Seed 15 [hp_X]/1 mL; Phosphorus 15 [hp_X]/1 mL; Pulsatilla Vulgaris 15 [hp_X]/1 mL; Spigelia Anthelmia 15 [hp_X]/1 mL; Sulfur 15 [hp_X]/1 mL; Matricaria Recutita 3 [hp_X]/1 mL; Echinacea, Unspecified 3 [hp_X]/1 mL; Ruta Graveolens Flowering Top 3 [hp_X]/1 mL; Taraxacum Officinale 3 [hp_X]/1 mL
INACTIVE INGREDIENTS: Alcohol

Doggy Breath

INDICATIONS & USAGE SECTION

Doggy Breath Formulated for symptoms associated with bad breath resulting from improper diet, indigestion or poor dental hygiene.

DOSAGE & ADMINISTRATION SECTION

Directions: Pets, under 50 lbs., give 3 drops by mouth (50 to 500 lbs. - 6 drops, over 500 lbs. - 1/2 teaspoon) one to four times daily or as directed by a health professional. Place in mouth or purified water.

OTC - ACTIVE INGREDIENT SECTION

Equal parts of Chamomilla 6x, Echinacea 6x, Iris versicolor 6x, Ruta 6x, Taraxacum 6x, Antimon. crud. 15x, Arsenicum alb. 15x, Baptisia 15x, Bryonia 15x, Carbo veg. 15x, Chelidonium majus 15x, Cinchona 15x, Colchicum 15x, Daphne indica 15x, Ipecac. 15x, Iris versicolor 15x, Kali carb. 15x, Kreosotum 15x, Lachesis 15x, Lycopodium 15x, Mag. carb. 15x, Merc. viv. 15x, Nux vom. 15x, Phosphorus 15x, Pulsatilla 15x, Spigelia anth. 15x, Sulphur 15x, Pyrogenium 30x.

OTC - PURPOSE SECTION

Formulated for symptoms associated with bad breath resulting from improper diet, indigestion or poor dental hygiene.

INACTIVE INGREDIENT SECTION

Inactive Ingredients: USP Purified Water; USP Gluten-free, non-GMO, organic cane dispensing alcohol 20%.

QUESTIONS SECTION

newtonlabs.net - Questions? 1.800.448.7256
Newton Laboratories, Inc. FDA Est # 1051203 - Conyers, GA 30013

WARNINGS SECTION

WARNINGS: Do not use if tamper-evident seal is broken or missing. If symptoms worsen or persist for more than a few days, consult a doctor. If pregnant or breast-feeding, ask a doctor before use.

OTC - PREGNANCY OR BREAST FEEDING SECTION

If pregnant or breast-feeding, ask a doctor before use.

OTC - KEEP OUT OF REACH OF CHILDREN SECTION

Keep out of reach of children.